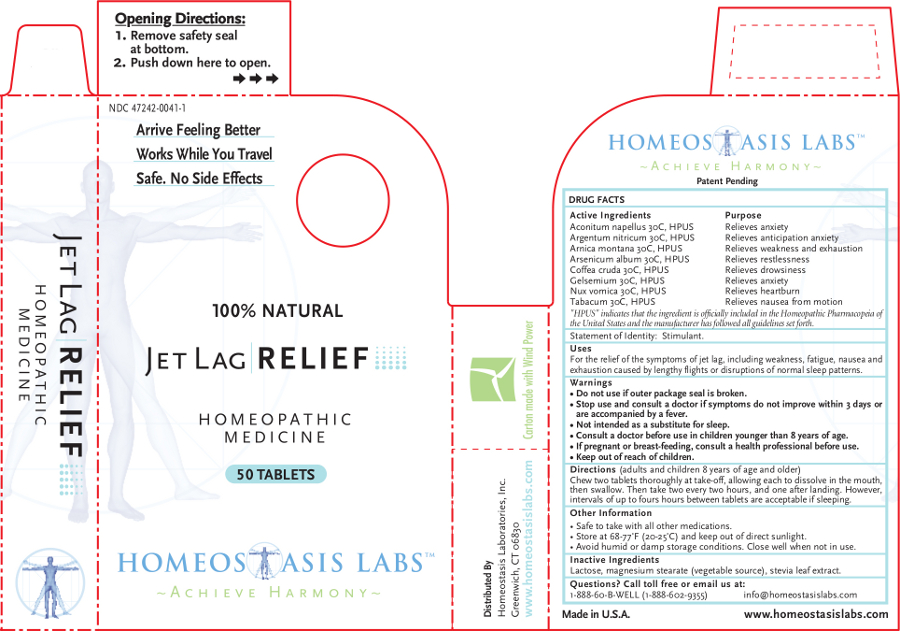 DRUG LABEL: Jet Lag RELIEF
NDC: 47242-0041 | Form: TABLET, CHEWABLE
Manufacturer: Homeostasis Laboratories, Inc.
Category: homeopathic | Type: HUMAN OTC DRUG LABEL
Date: 20121114

ACTIVE INGREDIENTS: ACONITUM NAPELLUS 30 [hp_C]/1 1; SILVER NITRATE 30 [hp_C]/1 1; ARNICA MONTANA 30 [hp_C]/1 1; ARSENIC TRIOXIDE 30 [hp_C]/1 1; ARABICA COFFEE BEAN 30 [hp_C]/1 1; GELSEMIUM SEMPERVIRENS ROOT 30 [hp_C]/1 1; STRYCHNOS NUX-VOMICA SEED 30 [hp_C]/1 1; TOBACCO LEAF 30 [hp_C]/1 1
INACTIVE INGREDIENTS: LACTOSE; MAGNESIUM STEARATE; STEVIA REBAUDIUNA LEAF

Jet Lag RELIEF

Active Ingredients | Purpose
Aconitum napellus 30C, HPUS | Relieves anxiety
Argentum nitricum 30C, HPUS | Relieves anticipation anxiety
Arnica montana 30C, HPUS | Relieves weakness and exhaustion
Arsenicum album 30C, HPUS | Relieves restlessness
Coffea cruda 30C, HPUS | Relieves drowsiness
Gelsemium 30C, HPUS | Relieves anxiety
Nux vomica 30C, HPUS | Relieves heartburn
Tabacum 30C, HPUS | Relieves nausea from motion

"HPUS" indicates that the ingredient is officially included in the Homeopathic Pharmacopeia of the United States and the manufacturer has followed all guidelines set forth.

Statement of Identity: Stimulant.

Uses

For the relief of the symptoms of jet lag, including weakness, fatigue, nausea and exhaustion caused by lengthy flights or disruptions of normal sleep patterns.

Warnings

- Do not use if outer package seal is broken.
- Stop use and consult a doctor if symptoms do not improve within 3 days or are accompanied by a fever.
- Not intended as a substitute for sleep.
- Consult a doctor before use in children younger than 8 years of age.

PREGNANCY OR BREAST FEEDING

- If pregnant or breast-feeding, consult a health professional before use.

- Keep out of reach of children.

Directions

(adults and children 8 years of age and older)

Chew two tablets thoroughly at take-off, allowing each to dissolve in the mouth, then swallow. Then take two every two hours, and one after landing. However, intervals of up to fours hours between tablets are acceptable if sleeping.

Other information

- Safe to take with all other medications.
- Store at 68-77°F (20-25°C) and keep out of direct sunlight.
- Avoid humid or damp storage conditions. Close well when not in use.

Inactive Ingredients

Lactose, magnesium stearate (vegetable source), stevia leaf extract.

Questions? Call toll free or email us at:

1-888-60-B-WELL (1-888-602-9355)

info@homeostasislabs.com